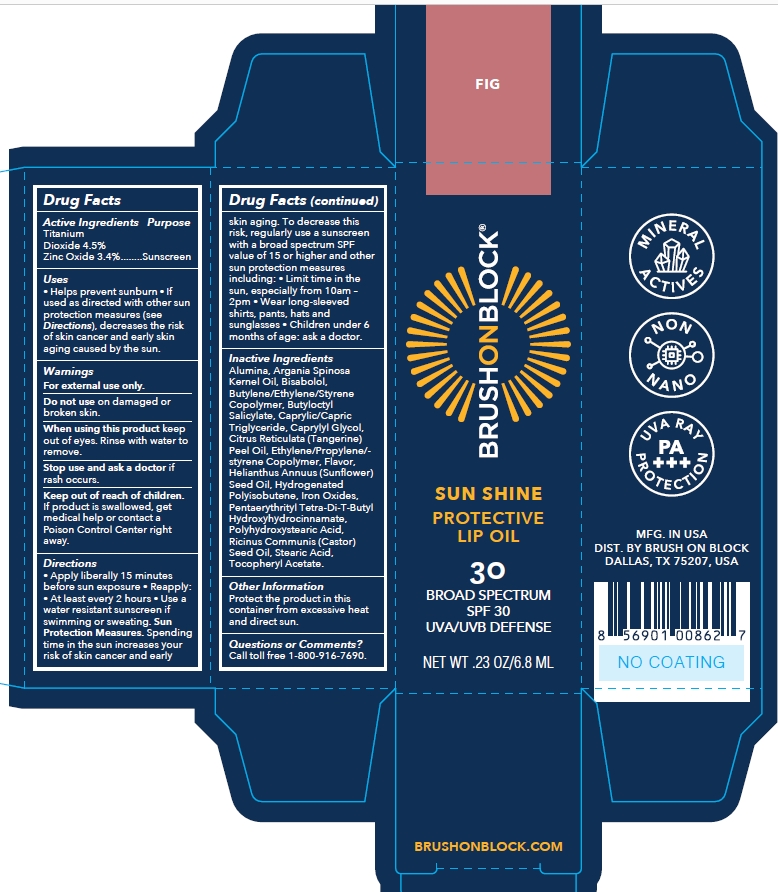 DRUG LABEL: Brush On Block Sun Shine SPF 30 Protective Lip Oil Fig
NDC: 58274-018 | Form: OIL
Manufacturer: SPF Ventures LLC
Category: otc | Type: HUMAN OTC DRUG LABEL
Date: 20240305

ACTIVE INGREDIENTS: TITANIUM DIOXIDE 4.5 g/100 mL; ZINC OXIDE 3.4 g/100 mL
INACTIVE INGREDIENTS: PENTAERYTHRITOL TETRAKIS(3-(3,5-DI-TERT-BUTYL-4-HYDROXYPHENYL)PROPIONATE); CASTOR OIL; STEARIC ACID; .ALPHA.-TOCOPHEROL ACETATE; FERRIC OXIDE RED; POLYHYDROXYSTEARIC ACID (2300 MW); ALUMINUM OXIDE; BUTYLOCTYL SALICYLATE; BUTYLATED HYDROXYTOLUENE; ARGAN OIL; LEVOMENOL; CAPRYLYL GLYCOL; MANDARIN OIL; SUNFLOWER OIL; HYDROGENATED POLYBUTENE (1300 MW); MEDIUM-CHAIN TRIGLYCERIDES; ETHYLHEXYL PALMITATE

Brush On Block Sun Shine SPF 30 Protective Lip Oil Fig

Active Ingredients

titanium dioxide 4.5%

zinc oxide 3.4%

Uses

- Helps prevent sunburn
- If used as directed with other sun protection measures (see Directions), decreases the risk of skin cancer and early skin aging caused by the sun.

Warnings

For external use only.

Do not use on damaged or broken skin

When using this product keep out of eyes. Rinse with water to remove.

Stop use and ask a doctor if rash occurs.

Keep out of reach of children

If product is swallowed, get medical help or contact a Poison Control Center right away.

Directions

- apply liberally 15 minutes before sun exposure.
- reapply at least every 2 hours
- use a water resistant sunscreen if swimming or sweating
- Children under 6 months of age: Ask a doctor.
- Sunprotection Measures. Spending time in the sun increases your risk of skin cancer and early skin aging. To decrease this risk, regularly use a sunscreen with a broad spectrum SPF value of 15 or higher and other sun protection measures including:
- limit time in the sun, especially from 10am-2pm

wear long-sleeved shirts, pants, hats and sunglasses.

Inactive Ingredients

ALUMINA

ARGANIA SPINOSA KERNEL OIL

BISABOLOL

BUTYLENE/ETHYLENE/STYRENE COPOLYMER

BUTYLOCTYL SALICYLATE

CAPRYLIC/CAPRIC TRIGLYCERIDE

CAPRYLYL GLYCOL

CITRUS RETICULATA (TANGERINE) PEEL OIL

ETHYLENE/PROPYLENE/STYRENE COPOLYMER

FLAVOR

HELIANTHUS ANNUUS (SUNFLOWER) SEED OIL

HYDROGENATED POLYISOBUTENE

IRON OXIDES

PENTAERYTHRITYL TETRA-DI-T-BUTYL HYDROXYHYDROCINNAMATE

POLYHYDROXYSTEARIC ACID

RICINUS COMMUNIS (CASTOR) SEED OIL

STEARIC ACID

TOCOPHERYL ACETATE

Other Information

Protect the product in this container from excessive heat and direct sun

Purpose

Sunscreen